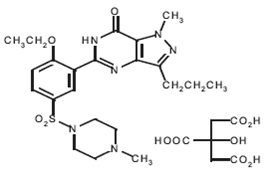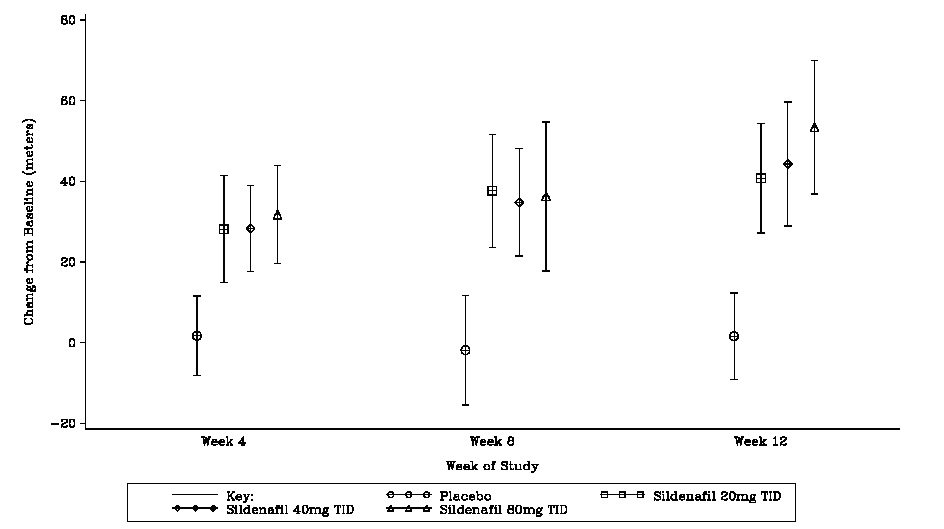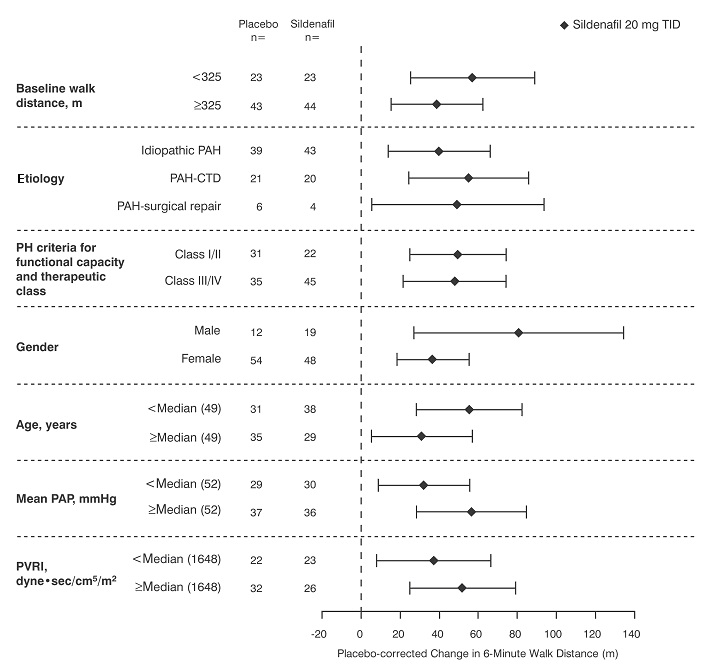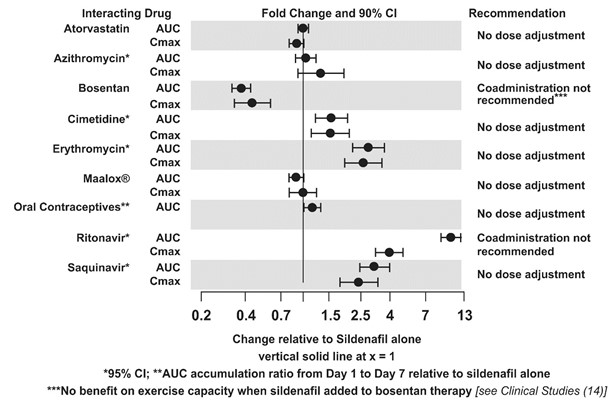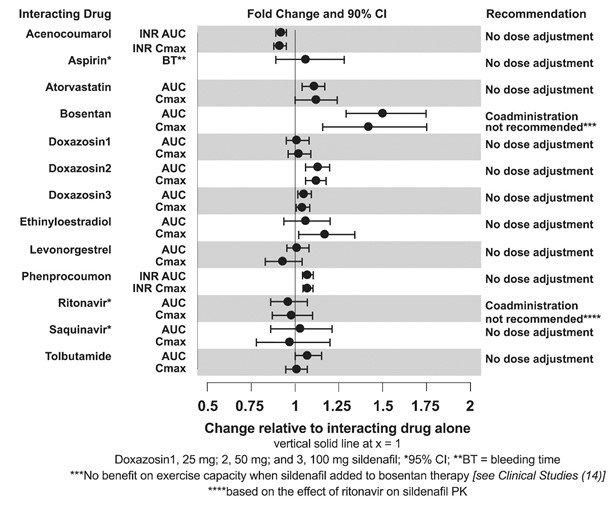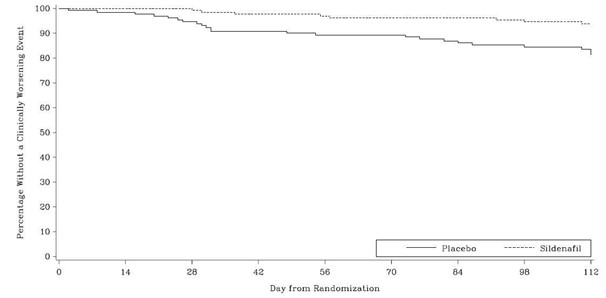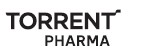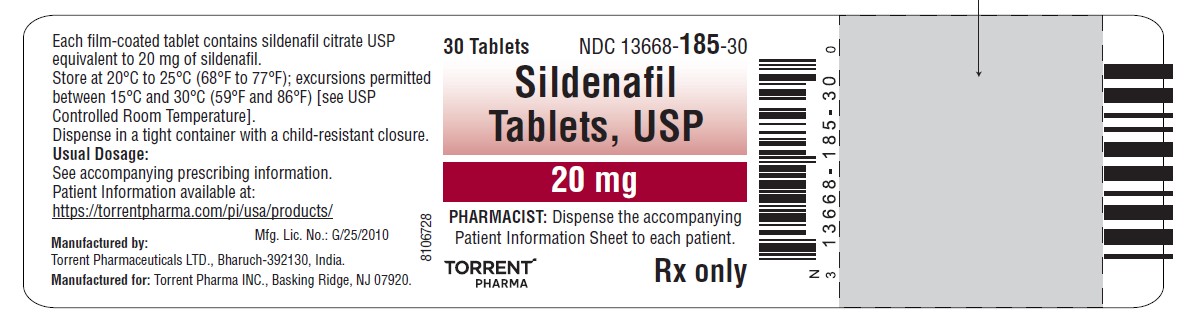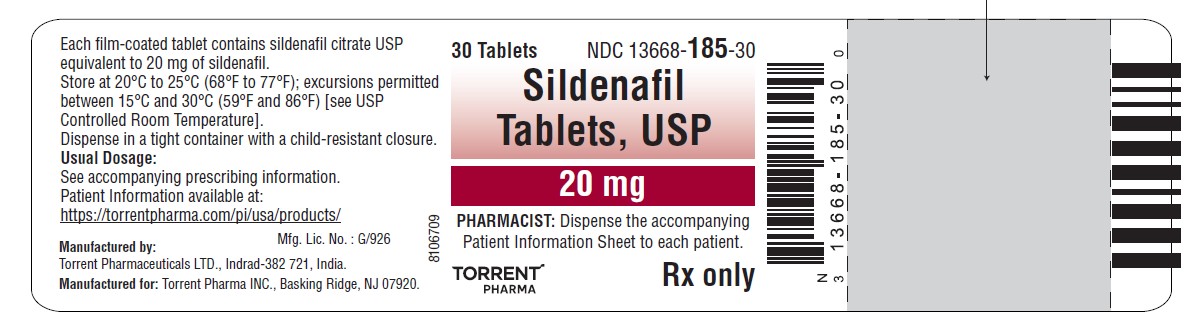 DRUG LABEL: Sildenafil
NDC: 13668-185 | Form: TABLET, FILM COATED
Manufacturer: Torrent Pharmaceuticals Limited
Category: prescription | Type: HUMAN PRESCRIPTION DRUG LABEL
Date: 20260209

ACTIVE INGREDIENTS: SILDENAFIL CITRATE 20 mg/1 1
INACTIVE INGREDIENTS: ANHYDROUS DIBASIC CALCIUM PHOSPHATE; CELLULOSE, MICROCRYSTALLINE; CROSCARMELLOSE SODIUM; HYPROMELLOSE 2910 (6 MPA.S); SODIUM STEARYL FUMARATE; TITANIUM DIOXIDE; TRIACETIN

HIGHLIGHTS OF PRESCRIBING INFORMATION

These highlights do not include all the information needed to use SILDENAFIL TABLETS safely and effectively. See full prescribing information for SILDENAFIL TABLETS.
SILDENAFIL tablets, for oral use
Initial U.S. Approval: 1998

RECENT MAJOR CHANGES

Indications and Usage (1) 1/2023
Dosage and Administration (2.1, 2.2) 1/2023

1 INDICATIONS AND USAGE

Adults
Sildenafil citrate is a phosphodiesterase-5 (PDE-5) inhibitor indicated for the treatment of pulmonary arterial hypertension (PAH) (World Health Organization [WHO] Group I) in adults to improve exercise ability and delay clinical worsening. (1)

2 DOSAGE AND ADMINISTRATION

• Adults: 20 mg three times a day. (2.1)

3 DOSAGE FORMS AND STRENGTHS

- Tablets: 20 mg (3)

4 CONTRAINDICATIONS

- Use with organic nitrates or riociguat. (4)
- History of hypersensitivity reaction to sildenafil or any component of the tablet. (4)

5 WARNINGS AND PRECAUTIONS

- Vasodilation effects may be more common in patients with hypotension or on antihypertensive therapy. (5.1)
- Use in pulmonary veno-occlusive disease (PVOD) may cause pulmonary edema and is not recommended. (5.2)
- Hearing or visual impairment: Seek medical attention if sudden decrease or loss of vision or hearing occurs. (5.4, 5.5)
- Pulmonary hypertension (PH) secondary to sickle cell disease: Sildenafil citrate may cause serious vaso-occlusive crises. (5.8)

6 ADVERSE REACTIONS

Adults: Headache, dyspepsia, flushing, pain in limb, myalgia, back pain and diarrhea. (6.1, 6.2)

To report SUSPECTED ADVERSE REACTIONS, contact Torrent Pharma Inc. at 1-800-912-9561 or FDA at 1-800-FDA-1088 or www.fda.gov/medwatch.

7 DRUG INTERACTIONS

• Use with strong CYP3A inhibitors: Not recommended. (7, 12.3)
• Concomitant PDE-5 inhibitors: Avoid use with Viagra® or other PDE-5 inhibitors. (5.6)

Pediatric use information is approved for Viatris Specialty LLC's, REVATIO (sildenafil) tablets. However, due to Viatris Specialty LLC's marketing exclusivity rights, this drug product is not labeled with that information.

FULL PRESCRIBING INFORMATION

1 INDICATIONS AND USAGE

Adults

Sildenafil tablets are indicated for the treatment of pulmonary arterial hypertension (PAH) (World Health Organization [WHO] Group I) in adults to improve exercise ability and delay clinical worsening [see Clinical Studies (14)].

Pediatric use information is approved for Viatris Specialty LLC's, REVATIO (sildenafil) tablets. However, due to Viatris Specialty LLC's marketing exclusivity rights, this drug product is not labeled with that information.

2 DOSAGE AND ADMINISTRATION

2.1 Recommended Dosage in Adults

Oral Dosage

The recommended dosage of sildenafil tablets are 20 mg three times a day. [see Clinical Studies (14)]

Pediatric use information is approved for Viatris Specialty LLC's, REVATIO (sildenafil) tablets. However, due to Viatris Specialty LLC's marketing exclusivity rights, this drug product is not labeled with that information.

3 DOSAGE FORMS AND STRENGTHS

Sildenafil Tablets, USP

Sildenafil tablets, USP are supplied as white to off-white, round, biconvex, film-coated tablets debossed with '85' on one side and plain on other side containing sildenafil citrate equivalent to 20 mg of sildenafil.

4 CONTRAINDICATIONS

Sildenafil citrate is contraindicated in patients with:

- Concomitant use of organic nitrates in any form, either regularly or intermittently, because of the greater risk of hypotension [see Warnings and Precautions (5.1)] .
- Concomitant use of riociguat, a guanylate cyclase stimulator. Phosphodiesterase-5 (PDE5) inhibitors, including sildenafil, may potentiate the hypotensive effects of riociguat.
- Known hypersensitivity to sildenafil or any component of the tablet. Hypersensitivity, including anaphylactic reaction, anaphylactic shock and anaphylactoid reaction, has been reported in association with the use of sildenafil.

5 WARNINGS AND PRECAUTIONS

5.1 Hypotension

Sildenafil citrate has vasodilatory properties, resulting in mild and transient decreases in blood pressure. Before prescribing sildenafil tablets, carefully consider whether patients with certain underlying conditions could be adversely affected by such vasodilatory effects (e.g., patients on antihypertensive therapy or with resting hypotension [blood pressure less than 90/50], fluid depletion, severe left ventricular outflow obstruction, or autonomic dysfunction). Monitor blood pressure when co-administering blood pressure lowering drugs with sildenafil citrate.

5.2 Worsening Pulmonary Vascular Occlusive Disease

Pulmonary vasodilators may significantly worsen the cardiovascular status of patients with pulmonary veno-occlusive disease (PVOD). Since there are no clinical data on administration of sildenafil citrate to patients with veno-occlusive disease, administration of sildenafil citrate to such patients is not recommended. Should signs of pulmonary edema occur when sildenafil citrate is administered, consider the possibility of associated PVOD.

5.3 Epistaxis

The incidence of epistaxis was 13% in patients taking sildenafil citrate with PAH secondary to CTD. This effect was not seen in idiopathic PAH (sildenafil 3%, placebo 2%) patients. The incidence of epistaxis was also higher in sildenafil-treated patients with a concomitant oral vitamin K antagonist (9% versus 2% in those not treated with concomitant vitamin K antagonist).

The safety of sildenafil citrate is unknown in patients with bleeding disorders or active peptic ulceration.

5.4 Visual Loss

When used to treat erectile dysfunction, non-arteritic anterior ischemic optic neuropathy (NAION), a cause of decreased vision including permanent loss of vision, has been reported postmarketing in temporal association with the use of PDE-5 inhibitors, including sildenafil. Most patients had underlying anatomic or vascular risk factors for developing NAION, including low cup to disc ratio (“crowded disc”).

Advise patients to seek immediate medical attention in the event of a sudden loss of vision in one or both eyes while taking sildenafil citrate.

There are no controlled clinical data on the safety or efficacy of sildenafil citrate in patients with retinitis pigmentosa, a minority of whom have genetic disorders of retinal phosphodiesterases. Therefore, use of sildenafil citrate in patients with retinitis pigmentosa is not recommended.

5.5 Hearing Loss

Cases of sudden decrease or loss of hearing, which may be accompanied by tinnitus and dizziness, have been reported in temporal association with the use of PDE-5 inhibitors, including sildenafil citrate. In some of the cases, medical conditions and other factors were reported that may have played a role. In many cases, medical follow-up information was limited. It is not possible to determine whether these reported events are related directly to the use of sildenafil citrate, to the patient's underlying risk factors for hearing loss, a combination of these factors, or to other factors.

Advise patients to seek prompt medical attention in the event of sudden decrease or loss of hearing while taking PDE-5 inhibitors, including sildenafil tablets.

5.6 Combination with other PDE-5 inhibitors

Sildenafil is also marketed as VIAGRA®. The safety and efficacy of combinations of sildenafil tablets with VIAGRA or other PDE-5 inhibitors have not been studied. Inform patients taking sildenafil tablets not to take VIAGRA or other PDE-5 inhibitors.

5.7 Priapism

Use sildenafil citrate with caution in patients with anatomical deformation of the penis (e.g., angulation, cavernosal fibrosis, or Peyronie's disease) or in patients who have conditions, which may predispose them to priapism (e.g., sickle cell anemia, multiple myeloma, or leukemia). In the event of an erection that persists longer than 4 hours, the patient should seek immediate medical assistance. If priapism (painful erection greater than 6 hours in duration) is not treated immediately, penile tissue damage and permanent loss of potency could result.

5.8 Vaso-occlusive Crisis in Patients with Pulmonary Hypertension Secondary to Sickle Cell Disease

In a small, prematurely terminated study of patients with pulmonary hypertension (PH) secondary to sickle cell disease, vaso-occlusive crises requiring hospitalization were more commonly reported by patients who received sildenafil citrate than by those randomized to placebo. The effectiveness and safety of sildenafil citrate in the treatment of PH secondary to sickle cell disease has not been established.

6 ADVERSE REACTIONS

The following serious adverse events are discussed elsewhere in the labeling:

- Hypotension [see Warnings and Precautions (5.1)]
- Vision Loss [see Warnings and Precautions (5.4)]
- Hearing Loss [see Warnings and Precautions (5.5)]
- Priapism [see Warnings and Precautions (5.7)]
- Vaso-occlusive Crisis in Patients with Pulmonary Hypertension Secondary to Sickle Cell Disease [see Warnings and Precautions (5.8) ]

6.1 Clinical Trials Experience

Because clinical trials are conducted under widely varying conditions, adverse reaction rates observed in the clinical trials of a drug cannot be directly compared to rates in the clinical trials of another drug and may not reflect the rates observed in practice.

In a 12-week, placebo-controlled clinical study and an open-label extension study (SUPER-1) in 277 sildenafil citrate-treated adults with PAH (WHO Group I) [see Clinical Studies (14)] the adverse reactions that were reported by at least 10% of sildenafil citrate-treated patients in any dosing group, and were more frequent in sildenafil citrate-treated patients than in placebo-treated patients are shown in Table 1. Adverse reactions were generally transient and mild to moderate in nature. The overall frequency of discontinuation in sildenafil citrate-treated patients was 3% (20 mg and 40 mg three times a day) and 8% (80 mg three times a day). The overall frequency of discontinuation for placebo was 3%.

Table 1. Most Common Adverse Reactions in Patients Treated with sildenafil tablets 20 mg, 40 mg, 80 mg and Placebo three times per day in SUPER-1 (More Frequent in sildenafil-Treated Patients than Placebo-Treated Patients)
 | Sildenafil tablets 20 mg (n = 69) | Sildenafil tablets 40 mg (n = 67) | Sildenafil tablets 80 mg (n = 71) | Placebo; (n = 70)
Headache | 46% | 42% | 49% | 39%
Flushing | 10% | 9% | 16% | 4%
Pain in Limb | 7% | 15% | 9% | 6%
Myalgia | 7% | 6% | 14% | 4%
Back Pain | 13% | 13% | 9% | 11%
Dyspepsia | 13% | 8% | 13% | 7%
Diarrhea | 9% | 12% | 10% | 6%

In a placebo-controlled fixed dose titration study (PACES-1) of sildenafil citrate (starting with recommended dose of 20 mg and increased to 40 mg and then 80 mg all three times a day) as an adjunct to intravenous epoprostenol in patients with PAH, no new safety issues were identified except for edema, which occurred in 25% of subjects in the combined sildenafil citrate + epoprostenol group compared with 13% of subjects in the epoprostenol group [see Clinical Studies (14)].

Pediatric use information is approved for Viatris Specialty LLC's, REVATIO (sildenafil) tablets. However, due to Viatris Specialty LLC's marketing exclusivity rights, this drug product is not labeled with that information.

6.2 Postmarketing Experience

The following adverse reactions have been identified during post approval use of sildenafil (marketed for both PAH and erectile dysfunction). Because these reactions are reported voluntarily from a population of uncertain size, it is not always possible to reliably estimate their frequency or establish a causal relationship to drug exposure.

Cardiovascular Events

In postmarketing experience with sildenafil at doses indicated for erectile dysfunction, serious cardiovascular, cerebrovascular, and vascular events, including myocardial infarction, sudden cardiac death, ventricular arrhythmia, cerebrovascular hemorrhage, transient ischemic attack, hypertension, pulmonary hemorrhage, and subarachnoid and intracerebral hemorrhages have been reported in temporal association with the use of the drug. Most, but not all, of these patients had preexisting cardiovascular risk factors. Many of these events were reported to occur during or shortly after sexual activity, and a few were reported to occur shortly after the use of sildenafil without sexual activity. Others were reported to have occurred hours to days after use concurrent with sexual activity. It is not possible to determine whether these events are related directly to sildenafil, to sexual activity, to the patient's underlying cardiovascular disease, or to a combination of these or other factors.

Nervous System

Seizure, seizure recurrence

Ophthalmologic

NAION [see Warnings and Precautions (5.4), Patient Counseling Information (17)].

7 DRUG INTERACTIONS

Nitrates

Concomitant use of sildenafil citrate with nitrates in any form is contraindicated [see Contraindications (4)] .

Strong CYP3A Inhibitors
Concomitant use of sildenafil citrate with strong CYP3A inhibitors is not recommended [see Clinical Pharmacology (12.3)].

Moderate-to-Strong CYP3A Inducers
Concomitant use of sildenafil citrate with moderate-to-strong CYP3A inducers (such as bosentan) decreases the sildenafil exposure. Dose up-titration of sildenafil citrate may be needed when initiating treatment with moderate-to-strong CYP3A inducers. Reduce the dose of sildenafil tablets to 20 mg three times a day when discontinuing treatment with moderate-to-strong CYP3A inducers [see Clinical Pharmacology (12.3) and Clinical Studies (14)].

8 USE IN SPECIFIC POPULATIONS

8.1 Pregnancy

Risk Summary
Limited published data from randomized controlled trials, case-controlled trials, and case series do not report a clear association with sildenafil and major birth defects, miscarriage, or adverse maternal or fetal outcomes when sildenafil is used during pregnancy. There are risks to the mother and fetus from untreated pulmonary arterial hypertension (see Clinical Considerations). Animal reproduction studies conducted with sildenafil showed no evidence of embryo-fetal toxicity or teratogenicity at doses up to 32-and 65-times the recommended human dose (RHD) of 20 mg three times a day in rats and rabbits, respectively (see Data).

The estimated background risk of major birth defects and miscarriage for the indicated population is unknown. All pregnancies have a background risk of birth defect, loss, or other adverse outcomes. In the U.S. general population, the estimated background risk of major birth defects and miscarriage in clinically recognized pregnancies is 2 to 4% and 15 to 20%, respectively.

Clinical Considerations
Disease-Associated Maternal and/or Embryo/Fetal Risk
Pregnant women with untreated pulmonary arterial hypertension are at risk for heart failure, stroke, preterm delivery, and maternal and fetal death.

Data
Animal Data
No evidence of teratogenicity, embryotoxicity, or fetotoxicity was observed in pregnant rats or rabbits dosed with sildenafil 200 mg/kg/day during organogenesis, a level that is, on a mg/m^2 basis, 32-and 65-times, respectively, the recommended human dose (RHD) of 20 mg three times a day. In a rat pre-and postnatal development study, the no-observed-adverse-effect dose was 30 mg/kg/day (equivalent to 5-times the RHD on a mg/m^2 basis).

8.2 Lactation

Risk Summary
Limited published data from a case report describe the presence of sildenafil and its active metabolite in human milk. There is insufficient information about the effects of sildenafil on the breastfed infant and no information on the effects of sildenafil on milk production. Limited clinical data during lactation preclude a clear determination of the risk of sildenafil citrate to an infant during lactation.

8.4 Pediatric Use

The safety and effectiveness of Sildenafil citrate have not been established in pediatric patients younger than 1 year of age.

Pediatric use information is approved for Viatris Specialty LLC's, REVATIO (sildenafil) tablets. However, due to Viatris Specialty LLC's marketing exclusivity rights, this drug product is not labeled with that information.

8.5 Geriatric Use

Clinical studies of sildenafil citrate did not include sufficient numbers of patients aged 65 and over to determine whether they respond differently from younger patients. Other reported clinical experience has not identified differences in responses between the elderly and younger patients. In general, dose selection for an elderly patient should be cautious, reflecting the greater frequency of decreased hepatic, renal, or cardiac function, and of concomitant disease or other drug therapy [see Clinical Pharmacology (12.3)] .

8.6 Patients with Hepatic Impairment

No dose adjustment for mild to moderate impairment is required. Severe impairment has not been studied [see Clinical Pharmacology (12.3)] .

8.7 Patients with Renal Impairment

No dose adjustment is required (including severe impairment CLcr <30 mL/min) [see Clinical Pharmacology (12.3)] .

10 OVERDOSAGE

In studies with healthy volunteers of single doses up to 800 mg, adverse events were similar to those seen at lower doses but rates and severities were increased.

In cases of overdose, standard supportive measures should be adopted as required. Renal dialysis is not expected to accelerate clearance as sildenafil is highly bound to plasma proteins and it is not eliminated in the urine.

11 DESCRIPTION

Sildenafil tablets, USP, phosphodiesterase-5 (PDE-5) inhibitor, is the citrate salt of sildenafil, a selective inhibitor of cyclic guanosine monophosphate (cGMP)-specific phosphodiesterase type-5 (PDE-5). Sildenafil is also marketed as VIAGRA® for erectile dysfunction.

Sildenafil citrate, USP is designated chemically as 1-[[3-(6,7-dihydro-1-methyl-7-oxo-3-propyl-1 H-pyrazolo [4,3- d] pyrimidin-5-yl)-4- ethoxyphenyl] sulfonyl]-4-methylpiperazine citrate and has the following structural formula:

Sildenafil citrate, USP is a white to off-white crystalline powder with a solubility of 3.5 mg/mL in water and a molecular weight of 666.7.

Sildenafil Tablets USP: Sildenafil citrate is formulated as white, film-coated round tablets for oral administration. Each tablet contains sildenafil citrate equivalent to 20 mg of sildenafil. In addition to the active ingredient, sildenafil citrate, each tablet contains the following inactive ingredients: croscarmellose sodium, dibasic calcium phosphate anhydrous, hypromellose, microcrystalline cellulose, sodium stearyl fumarate, titanium dioxide and triacetin.

12 CLINICAL PHARMACOLOGY

12.1 Mechanism of Action

Sildenafil is an inhibitor of cGMP specific PDE-5 in the smooth muscle of the pulmonary vasculature, where PDE-5 is responsible for degradation of cGMP. Sildenafil, therefore, increases cGMP within pulmonary vascular smooth muscle cells resulting in relaxation. In patients with PAH, this can lead to vasodilation of the pulmonary vascular bed and, to a lesser degree, vasodilatation in the systemic circulation.

Studies in vitro have shown that sildenafil is selective for PDE5. Its effect is more potent on PDE-5 than on other known phosphodiesterases (10-fold for PDE6, greater than 80-fold for PDE1, greater than 700-fold for PDE2, PDE3, PDE4, PDE7, PDE8, PDE9, PDE10, and PDE11). The approximately 4,000-fold selectivity for PDE5 versus PDE3 is important because PDE3 is involved in control of cardiac contractility. Sildenafil is only about 10-times as potent for PDE5 compared to PDE6, an enzyme found in the retina and involved in the phototransduction pathway of the retina. This lower selectivity is thought to be the basis for abnormalities related to color vision observed with higher doses or plasma levels [see Clinical Pharmacology (12.2)] .

In addition to pulmonary vascular smooth muscle and the corpus cavernosum, PDE5 is also found in other tissues including vascular and visceral smooth muscle and in platelets. The inhibition of PDE5 in these tissues by sildenafil may be the basis for the enhanced platelet anti-aggregatory activity of nitric oxide observed in vitro, and the mild peripheral arterial-venous dilatation in vivo.

12.2 Pharmacodynamics

Effects of Sildenafil Citrate on Hemodynamic Measures

Adults

Patients on all sildenafil citrate doses achieved a statistically significant reduction in mean pulmonary arterial pressure (mPAP) compared to those on placebo in a study with no background vasodilators [see SUPER-1 in Clinical Studies (14)]. Data on other hemodynamic measures for the sildenafil tablets 20 mg three times a day and placebo dosing regimens is displayed in Table 2. The relationship between these effects and improvements in 6-minute walk distance is unknown.

Table 2. Changes from Baseline in Hemodynamic Parameters at Week 12 [mean (95% CI)] for the Sildenafil Tablets 20 mg Three Times a Day and Placebo Group
 | Placebo (n = 65)* | Sildenafil Tablets 20 mg (n = 65)*
mPAP (mmHg) | 0.6 (-0.8, 2.0) | -2.1 (-4.3, 0.0)
PVR (dyn.s/cm^5) | 49 (-54, 153) | -122 (-217, -27)
SVR (dyn.s/cm^5) | -78 (-197, 41) | -167 (-307, -26)
RAP (mmHg) | 0.3 (-0.9, 1.5) | -0.8 (-1.9, 0.3)
CO (L/min) | -0.1 (-0.4, 0.2) | 0.4 (0.1, 0.7)
HR (beats/min) | -1.3 (-4.1, 1.4) | -3.7 (-5.9, -1.4)
mPAP = mean pulmonary arterial pressure; PVR= pulmonary vascular resistance; SVR = systemic vascular resistance; RAP = right atrial pressure; CO = cardiac output; HR = heart rate
* The number of patients per treatment group varied slightly for each parameter due to missing assessments.

Effects of Sildenafil Citrate on Blood Pressure

Single oral doses of sildenafil 100 mg administered to healthy volunteers produced decreases in supine blood pressure (mean maximum decrease in systolic/diastolic blood pressure of 8/5 mmHg). The decrease in blood pressure was most notable approximately 1 to 2 hours after dosing and was not different from placebo at 8 hours. Similar effects on blood pressure were noted with 25 mg, 50 mg and 100 mg doses of sildenafil, therefore the effects are not related to dose or plasma levels within this dosage range. Larger effects were recorded among patients receiving concomitant nitrates [see Contraindications (4)] .

Single oral doses of sildenafil up to 100 mg in healthy volunteers produced no clinically relevant effects on electrocardiogram (ECG). After chronic dosing of 80 mg three times a day to patients with PAH, no clinically relevant effects on ECG were reported.

After chronic dosing of 80 mg three times a day sildenafil to healthy volunteers, the largest mean change from baseline in supine systolic and supine diastolic blood pressures was a decrease of 9.0 mmHg and 8.4 mmHg, respectively.

After chronic dosing of 80 mg three times a day sildenafil to patients with systemic hypertension, the mean change from baseline in systolic and diastolic blood pressures was a decrease of 9.4 mmHg and 9.1 mmHg, respectively.

After chronic dosing of 80 mg three times a day sildenafil to patients with PAH, lesser reductions than above in systolic and diastolic blood pressures were observed (a decrease in both of 2 mmHg).

Effects of Sildenafil Citrate on Vision

At single oral doses of 100 mg and 200 mg, transient dose-related impairment of color discrimination (blue/green) was detected using the Farnsworth-Munsell 100-hue test, with peak effects near the time of peak plasma levels. This finding is consistent with the inhibition of PDE6, which is involved in phototransduction in the retina. An evaluation of visual function at doses up to 200 mg revealed no effects of sildenafil citrate on visual acuity, intraocular pressure, or pupillometry.

Pediatric use information is approved for Viatris Specialty LLC's, REVATIO (sildenafil) tablets. However, due to Viatris Specialty LLC's marketing exclusivity rights, this drug product is not labeled with that information.

12.3 Pharmacokinetics

Absorption and Distribution

Sildenafil citrate is rapidly absorbed after oral administration, with a mean absolute bioavailability of 41% (25 to 63%). Maximum observed plasma concentrations are reached within 30 to 120 minutes (median 60 minutes) of oral dosing in the fasted state. When sildenafil tablet is taken with a high-fat meal, the rate of absorption is reduced, with a mean delay in T max of 60 minutes and a mean reduction in Cmax of 29%. The mean steady state volume of distribution (Vss) for sildenafil is 105 L, indicating distribution into the tissues. Sildenafil and its major circulating N-desmethyl metabolite are both approximately 96% bound to plasma proteins. Protein binding is independent of total drug concentrations.

Bioequivalence was established between the 20 mg tablet and the 10 mg/mL oral suspension when administered as a 20 mg single oral dose of sildenafil (as citrate).

Metabolism and Excretion

Sildenafil is cleared predominantly by the CYP3A (major route) and cytochrome P450 2C9 (CYP2C9, minor route) hepatic microsomal isoenzymes. The major circulating metabolite results from N-desmethylation of sildenafil, and is, itself, further metabolized. This metabolite has a phosphodiesterase selectivity profile similar to sildenafil and an in vitro potency for PDE-5 approximately 50% of the parent drug. In healthy volunteers, plasma concentrations of this metabolite are approximately 40% of those seen for sildenafil, so that the metabolite accounts for about 20% of sildenafil's pharmacologic effects. In patients with PAH, however, the ratio of the metabolite to sildenafil is higher. Both sildenafil and the active metabolite have terminal half-lives of about 4 hours.

After either oral or intravenous administration, sildenafil is excreted as metabolites predominantly in the feces (approximately 80% of the administered oral dose) and to a lesser extent in the urine (approximately 13% of the administered oral dose).

Population Pharmacokinetics

Age, gender, race, and renal and hepatic function were included as factors assessed in the population pharmacokinetic model to evaluate sildenafil pharmacokinetics in patients with PAH. The dataset available for the population pharmacokinetic evaluation contained a wide range of demographic data and laboratory parameters associated with hepatic and renal function. None of these factors had a significant impact on sildenafil pharmacokinetics in patients with PAH.

In patients with PAH, the average steady-state concentrations were 20 to 50% higher when compared to those of healthy volunteers. There was also a doubling of Cmin levels compared to healthy volunteers. Both findings suggest a lower clearance and/or a higher oral bioavailability of sildenafil in patients with PAH compared to healthy volunteers.

Pediatric Patients

Pediatric use information is approved for Viatris Specialty LLC's, REVATIO (sildenafil) tablets. However, due to Viatris Specialty LLC's marketing exclusivity rights, this drug product is not labeled with that information.

Geriatric Patients

Healthy elderly volunteers (65 years or over) had a reduced clearance of sildenafil, resulting in approximately 84% and 107% higher plasma concentrations of sildenafil and its active N-desmethyl metabolite, respectively, compared to those seen in healthy younger volunteers (18 to 45 years). Due to age-differences in plasma protein binding, the corresponding increase in the AUC of free (unbound) sildenafil and its active N-desmethyl metabolite were 45% and 57%, respectively.

Renal Impairment

In volunteers with mild (CLcr = 50 to 80 mL/min) and moderate (CLcr = 30 to 49 mL/min) renal impairment, the pharmacokinetics of a single oral dose of sildenafil (50 mg) was not altered. In volunteers with severe (CLcr less than 30 mL/min) renal impairment, sildenafil clearance was reduced, resulting in approximately doubling of AUC and C max compared to age-matched volunteers with no renal impairment. In addition, N-desmethyl metabolite AUC and C max values were significantly increased 200% and 79%, respectively, in patients with severe renal impairment compared to patients with normal renal function.

Hepatic Impairment

In volunteers with mild to moderate hepatic cirrhosis (Child-Pugh class A and B), sildenafil clearance was reduced, resulting in increases in AUC (84%) and Cmax (47%) compared to age-matched volunteers with no hepatic impairment. Patients with severe hepatic impairment (Child-Pugh class C) have not been studied.

Drug Interaction Studies

In vitro studies

Sildenafil metabolism is principally mediated by the CYP3A (major route) and CYP2C9 (minor route) cytochrome P450 isoforms. Therefore, inhibitors of these isoenzymes may reduce sildenafil clearance and inducers of these isoenzymes may increase sildenafil clearance.

Sildenafil is a weak inhibitor of the cytochrome P450 isoforms 1A2, 2C9, 2C19, 2D6, 2E1 and 3A (IC50greater than 150 µM).

Sildenafil is not expected to affect the pharmacokinetics of compounds which are substrates of these CYP enzymes at clinically relevant concentrations.

In vivo studies

The effects of other drugs on sildenafil pharmacokinetics and the effects of sildenafil on the exposure to other drugs are shown in Figure 1 and Figure 2, respectively.

Figure 1. Effects of Other Drugs on Sildenafil Pharmacokinetics

Figure 2. Effects of Sildenafil on Other Drugs

CYP3A Inhibitors and Beta Blockers

Population pharmacokinetic analysis of data from patients in clinical trials indicated an approximately 30% reduction in sildenafil clearance when it was co-administered with mild/moderate CYP3A inhibitors and an approximately 34% reductions in sildenafil clearance when co-administered with beta-blockers. Sildenafil exposure at a dose of 80 mg three times a day without concomitant medication is shown to be 5-fold the exposure at a dose of 20 mg three times a day. This concentration range covers the same increased sildenafil exposure observed in specifically-designed drug interaction studies with CYP3A inhibitors (except for potent inhibitors such as ketoconazole, itraconazole, and ritonavir).

CYP3A4 Inducers Including Bosentan

Concomitant administration of strong CYP3A inducers is expected to cause substantial decreases in plasma levels of sildenafil.

Population pharmacokinetic analysis of data from patients in clinical trials indicated approximately 3-fold the sildenafil clearance when it was co-administered with mild CYP3A inducers.

Epoprostenol

The mean reduction of sildenafil (80 mg three times a day) bioavailability when co-administered with epoprostenol was 28%, resulting in about 22% lower mean average steady state concentrations. Therefore, the slight decrease of sildenafil exposure in the presence of epoprostenol is not considered clinically relevant. The effect of sildenafil on epoprostenol pharmacokinetics is not known.

No significant interactions were shown with tolbutamide (250 mg) or warfarin (40 mg), both of which are metabolized by CYP2C9.

Alcohol

Sildenafil (50 mg) did not potentiate the hypotensive effect of alcohol in healthy volunteers with mean maximum blood alcohol levels of 0.08%.

13 NONCLINICAL TOXICOLOGY

13.1 Carcinogenesis, Mutagenesis, Impairment of Fertility

Sildenafil was not carcinogenic when administered to rats for up to 24 months at 60 mg/kg/day, a dose resulting in total systemic exposure (AUC) to unbound sildenafil and its major metabolite 33- and 37-times, for male and female rats, respectively, the human exposure at the RHD of 20 mg three times a day. Sildenafil was not carcinogenic when administered to male and female mice for up to 21 and 18 months, respectively, at doses up to a maximally tolerated level of 10 mg/kg/day, a dose equivalent to the RHD on a mg/m^2 basis.

Sildenafil was negative in in vitro bacterial and Chinese hamster ovary cell assays to detect mutagenicity, and in vitro human lymphocytes and in vivo mouse micronucleus assays to detect clastogenicity.

There was no impairment of fertility in male or female rats given up to 60 mg sildenafil/kg/day, a dose producing a total systemic exposure (AUC) to unbound sildenafil and its major metabolite of 19- and 38-times for males and females, respectively, the human exposure at the RHD of 20 mg three times a day.

14 CLINICAL STUDIES

SUPER-1 (NCT00644605) - Sildenafil citrate monotherapy [20 mg, 40 mg, and 80 mg three times a day]

A randomized, double-blind, placebo-controlled study of sildenafil citrate (SUPER-1) was conducted in 277 patients with PAH (defined as a mean pulmonary artery pressure≥25 mmHg at rest with a pulmonary capillary wedge pressure<15 mmHg). Patients were predominantly WHO Functional Classes II-III. Allowed background therapy included a combination of anticoagulants, digoxin, calcium channel blockers, diuretics, and oxygen. The use of prostacyclin analogues, endothelin receptor antagonists, and arginine supplementation were not permitted. Patients who had failed to respond to bosentan were also excluded. Patients with left ventricular ejection fraction less than 45% or left ventricular shortening fraction less than 0.2 also were not studied.

Patients were randomized to receive placebo (n=70) or sildenafil tablet 20 mg (n = 69), 40 mg (n = 67) or 80 mg (n = 71) three times a day for a period of 12 weeks. They had either primary pulmonary hypertension (PPH) (63%), PAH associated with CTD (30%), or PAH following surgical repair of left-to-right congenital heart lesions (7%). The study population consisted of 25% men and 75% women with a mean age of 49 years (range: 18 to 81 years) and baseline 6-minute walk distance between 100 and 450 meters (mean 343).

The primary efficacy endpoint was the change from baseline at Week 12 (at least 4 hours after the last dose) in the 6-minute walk distance. Placebo-corrected mean increases in walk distance of 45 to 50 meters were observed with all doses of sildenafil citrate. These increases were significantly different from placebo, but the sildenafil citrate dose groups were not different from each other (see Figure 3), indicating no additional clinical benefit from doses higher than 20 mg three times a day. The improvement in walk distance was apparent after 4 weeks of treatment and was maintained at Week 8 and Week 12.

Figure 3. Change from Baseline in 6-Minute Walk Distance (meters) at Weeks 4, 8, and 12 in SUPER-1: Mean (95% Confidence Interval)

Figure 4 displays subgroup efficacy analyses in SUPER-1 for the change from baseline in 6-Minute Walk Distance at Week 12 including baseline walk distance, disease etiology, functional class, gender, age, and hemodynamic parameters.

Figure 4. Placebo-Corrected Change From Baseline in 6-Minute Walk Distance (meters) at Week 12 by Study Subpopulation in SUPER-1: Mean (95% Confidence Interval)

Key: PAH = pulmonary arterial hypertension; CTD = connective tissue disease; PH = pulmonary hypertension; PAP = pulmonary arterial pressure; PVRI = pulmonary vascular resistance index; TID = three times daily.

SUPER-2 (NCT00159887) Long-term Treatment of PAH

In a long-term follow-up of patients who were treated with sildenafil (n=277), K-M estimates of survival at 1, 2, and 3 years were 94%, 88% , and 79%, respectively. These uncontrolled observations do not allow comparison with a group not given sildenafil and cannot be used to determine the long term-effect of sildenafil on mortality.

PACES-1 (NCT00159861) - Sildenafil citrate Co-administered with Epoprostenol

A randomized, double-blind, placebo-controlled study (PACES-1) was conducted in 267 patients with PAH who were taking stable doses of intravenous epoprostenol. Patients had to have a mean pulmonary artery pressure (mPAP) greater than or equal to 25 mmHg and a pulmonary capillary wedge pressure (PCWP) less than or equal to 15 mmHg at rest via right heart catheterization within 21 days before randomization, and a baseline 6-minute walk test distance greater than or equal to 100 meters and less than or equal to 450 meters (mean 349 meters). Patients were randomized to placebo or sildenafil citrate (in a fixed titration starting from 20 mg to 40 mg and then 80 mg, three times a day) and all patients continued intravenous epoprostenol therapy.

At baseline patients had PPH (80%) or PAH secondary to CTD (20%);WHO Functional Class I (1%), II (26%), III (67%), or IV (6%); and the mean age was 48 years, 80% were female, and 79% were Caucasian.

There was a statistically significant greater increase from baseline in 6-minute walk distance at Week 16 (primary endpoint) for the sildenafil citrate group compared with the placebo group. The mean change from baseline at Week 16 (last observation carried forward) was 30 meters for the sildenafil tablet group compared with 4 meters for the placebo group giving an adjusted treatment difference of 26 meters (95% CI: 10.8, 41.2) (p = 0.0009).

Patients on sildenafil citrate achieved a statistically significant reduction in mPAP compared to those on placebo. A mean placebo-corrected treatment effect of -3.9 mmHg was observed in favor of sildenafil tablet (95% CI: -5.7, -2.1) (p = 0.00003).

Time to clinical worsening of PAH was defined as the time from randomization to the first occurrence of a clinical worsening event (death, lung transplantation, initiation of bosentan therapy, or clinical deterioration requiring a change in epoprostenol therapy). Table 4 displays the number of patients with clinical worsening events in PACES-1. Kaplan-Meier estimates and a stratified log-rank test demonstrated that placebo-treated patients were 3 times more likely to experience a clinical worsening event than sildenafil citrate -treated patients and that sildenafil citrate -treated patients experienced a significant delay in time to clinical worsening versus placebo-treated patients (p = 0.0074). Kaplan- Meier plot of time to clinical worsening is presented in Figure 5.

Table 4. Clinical Worsening Events in PACES-1
 | Placebo; (N = 131) |  | Sildenafil citrate; (N = 134)
Number of patients with clinical worsening first event | 23 |  | 8
 | First Event | All Events | First Event | All Events
Death, n | 3 | 4 | 0 | 0
Lung transplantation, n | 1 | 1 | 0 | 0
Hospitalization due to PAH, n | 9 | 11 | 8 | 8
Clinical deterioration resulting in: Change of Epoprostenol Dose, n Initiation of Bosentan, n | 9 1 | 16 1 | 0 0 | 2 0
Proportion worsened 95% Confidence Interval | 0.187 (0.12 to 0.26) |  | 0.062 (0.02 to 0.10)

Figure 5. Kaplan-Meier Plot of Time (in Days) to Clinical Worsening of PAH in PACES-1

Improvements in WHO Functional Class for PAH were also demonstrated in patients on sildenafil tablet compared to placebo. More than twice as many sildenafil citrate-treated patients (36%) as placebo-treated patients (14%) showed an improvement in at least one functional New York Heart Association (NYHA) class for PAH.

Study A1481243 (NCT00323297) – Sildenafil citrate Added to Bosentan Therapy – Lack of Effect on Exercise Capacity

A randomized, double-blind, placebo-controlled study was conducted in 103 patients with PAH who were on bosentan therapy for a minimum of 3 months. The PAH patients included those with primary PAH and PAH associated with CTD. Patients were randomized to placebo or sildenafil (20 mg three times a day) in combination with bosentan (62.5 to 125 mg twice a day). The primary efficacy endpoint was the change from baseline at Week 12 in 6-minute walk distance (6MWD). The results indicate that there is no significant difference in mean change from baseline on 6MWD observed between sildenafil 20 mg plus bosentan and bosentan alone.

Pediatric use information is approved for Viatris Specialty LLC's, REVATIO (sildenafil) tablets. However, due to Viatris Specialty LLC's marketing exclusivity rights, this drug product is not labeled with that information.

16 HOW SUPPLIED/STORAGE AND HANDLING

Sildenafil 20 mg tablets USP are white to off-white, round biconvex film coated tablets debossed with '85' on one side and plain on other side.

Bottles of 30 with child-resistant closure NDC 13668-185-30

Bottles of 90 with child-resistant closure NDC 13668-185-90

Bottles of 500 NDC 13668-185-05

Bottles of 1000 NDC 13668-185-10

Bottles of 5000 NDC 13668-185-51

Recommended Storage for Sildenafil Tablets USP: Store at 20°C to 25°C (68°F to 77°F); excursions permitted between 15°C and 30°C (59°F and 86°F) [see USP Controlled Room Temperature].

17 PATIENT COUNSELING INFORMATION

Advise the patient to read the FDA-approved patient labeling (Patient Information).

• Inform patients of contraindication of sildenafil tablets with regular and/or intermittent use of organic nitrates.

• Inform patients that sildenafil is also marketed as VIAGRA for erectile dysfunction. Advise patients taking sildenafil tablets not to take VIAGRA or other PDE-5 inhibitors.

• Advise patients to seek immediate medical attention for a sudden loss of vision in one or both eyes while taking sildenafil tablets. Such an event may be a sign of NAION.

• Advise patients to seek prompt medical attention in the event of sudden decrease or loss of hearing while taking sildenafil tablets. These events may be accompanied by tinnitus and dizziness.

Trademarks are the property of their respective owners.

Manufactured by:

Torrent Pharmaceuticals LTD., India.

Manufactured for:

Torrent Pharma INC., Basking Ridge, NJ 07920.

8106705 Revised: January 2026

PATIENT INFORMATION

Sildenafil (sil DEN a fil) Tablets USP

What is the most important information I should know about Sildenafil tablets?

Never take Sildenafil tablets with any nitrate or guanylate cyclase stimulator medicines.

- Your blood pressure could drop quickly to an unsafe level. Nitrates include:
- Medicines that treat chest pain (angina)
- Nitroglycerin in any form including tablets, patches, sprays, and ointments
- Isosorbide mononitrate or dinitrate
- Street drugs called “poppers” (amyl nitrate, butyl nitrate or nitrite)

Guanylate cyclase stimulators include:

- Riociguat, a medicine that treats pulmonary arterial hypertension and chronic thromboembolic pulmonary hypertension.

Ask your healthcare provider or pharmacist if you are not sure if you are taking a nitrate or a guanylate cyclase stimulator medicine.

See “What are the possible side effects of Sildenafil tablets?” for more information about side effects.

What are Sildenafil tablets?

Sildenafil tablets are prescription medicine used to treat pulmonary arterial hypertension (PAH). PAH is a type of high blood pressure in the arteries of your lungs. Sildenafil tablets may be used in:

- adults to improve your ability to exercise and help slow down the worsening of your physical condition.

It is not known if Sildenafil tablets are safe and effective in children younger than 1 year of age.

Do not take Sildenafil tablets if you:

- take medicines called nitrates.
- take riociguat, a guanylate cyclase stimulator medicine.
- are allergic to sildenafil or any of the ingredients in Sildenafil tablets. See the end of this leaflet for a complete list of ingredients in Sildenafil tablets.

Before taking Sildenafil tablets, tell your healthcare provider about all of your medical conditions, including if you:

- have low blood pressure
- have heart problems
- have pulmonary veno-occlusive disease (PVOD)
- have bleeding problems or a stomach (peptic) ulcer. It is not known if Sildenafil tablets are safe in people with bleeding problems or who have a stomach ulcer.
- have an eye problem called retinitis pigmentosa
- have ever had sudden loss of vision in one or both eyes, including an eye problem called non-arteritic anterior ischemic optic neuropathy (NAION)
- have ever had hearing problems such as ringing in the ears, dizziness, or loss of hearing
- have a deformed penis shape or Peyronie’s disease
- have any blood cell problems such as sickle cell anemia
- are pregnant or plan to become pregnant. It is not known if sildenafil tablets will harm your unborn baby.
- are breastfeeding or plan to breastfeed. Sildenafil citrate passes into your breast milk. It is not known if it can harm your baby. Talk with your healthcare provider about the best way to feed your baby during treatment with sildenafil tablets.

Tell your healthcare provider about all of the medicines you take, including prescription and over-the-counter medicines, vitamins, and herbal supplements. Sildenafil tablets and certain other medicines may affect each other and can cause side effects.

Especially tell your healthcare provider if you take:

nitrates or guanylate cyclase stimulators. See “What is the most important information I should know about sildenafil tablets?”

- medicines to treat high blood pressure
- medicines for erectile dysfunction (impotence). Sildenafil tablets contain sildenafil, which is the same medicine found in another medicine called VIAGRA®.VIAGRA is used for the treatment of erectile dysfunction. Do not take VIAGRA or other PDE-5 inhibitors during treatment with sildenafil tablets.

Ask your healthcare provider or pharmacist for a list of these medicines if you are not sure.

Know the medicines you take. Keep a list of your medicines and show it to your healthcare provider and pharmacist when you get a new medicine.

How should I take Sildenafil tablets?

- Take or give Sildenafil tablets exactly as your healthcare provider tells you.
- Your healthcare provider may change your dose of Sildenafil tablets as needed. Do not change your dose or stop taking Sildenafil tablets without talking to your healthcare provider.
- Take your prescribed dose of Sildenafil tablets 3 times a day.
- If you take too much Sildenafil tablets, call your healthcare provider or go to the nearest hospital emergency room right away.

What are the possible side effects of Sildenafil tablets?

Sildenafil tablets may cause serious side effects, including:

- See “What is the most important information I should know about Sildenafil tablets?”
- Decreased blood pressure. Sildenafil tablets may cause low blood pressure that last for a short time. If you take medicines to treat high blood pressure, your healthcare provider should monitor your blood pressure during treatment with Sildenafil tablets.
- Decreased eyesight or permanent loss of vision in one or both eyes can be a sign of non-arteritic anterior ischemic optic neuropathy (NAION). Most people who develop NAION have certain risk factors. You can ask your healthcare provider if you have questions about risk factors for NAION. If you notice a sudden decrease or loss of vision in one or both eyes during treatment with Sildenafil tablets, contact your healthcare provider right away.
- Sudden decrease or loss of hearing, sometimes with ringing in the ears and dizziness. If you notice a sudden decrease or loss of hearing during treatment with Sildenafil tablets, contact your healthcare provider right away.
- In men, an erection that lasts for more than 4 hours (priapism). If you have an erection, with or without pain, that lasts more than 4 hours, contact your healthcare provider or get emergency medical help right away. A painful erection that lasts more than 6 hours must be treated right away or you can have lasting damage to your penis, including the inability to have erections.

The most common side effects of Sildenafil tablets in adults include:

- nosebleeds • muscle aches and pain
- headache • back pain
- upset stomach • diarrhea
- getting red or hot in the face (flushing)
- arm or leg pain

These are not all the possible side effects of Sildenafil tablets.

Call your doctor for medical advice about side effects. You may report side effects to FDA at 1-800-FDA-1088.

How should I store Sildenafil tablets?

- Store Sildenafil tablets at room temperature between 68°F to 77°F (20°C to 25°C).

Keep Sildenafil tablets and all medicines out of the reach of children.

General information about the safe and effective use of Sildenafil tablets.

Medicines are sometimes prescribed for purposes other than those listed in a Patient Information leaflet. Do not use Sildenafil tablets for a condition for which it was not prescribed. Do not give Sildenafil tablets to other people, even if they have the same symptoms that you have. It may harm them. You can ask your healthcare provider or pharmacist for information about Sildenafil tablets that is written for health professionals.

What are the ingredients in Sildenafil tablets?

Active ingredients: sildenafil citrate, USP

Inactive ingredients:

Sildenafil tablets: croscarmellose sodium, dibasic calcium phosphate anhydrous, hypromellose, microcrystalline cellulose, sodium stearyl fumarate, titanium dioxide and triacetin.

Pediatric use information is approved for Viatris Specialty LLC's, REVATIO (sildenafil) tablets. However, due to Viatris Specialty LLC's marketing exclusivity rights, this drug product is not labeled with that information.

Trademarks are the property of their respective owners.

For more information call Torrent Pharma Inc. at 1-800-912-9561.

Manufactured by:

Torrent Pharmaceuticals LTD., India.

Manufactured for:

Torrent Pharma INC., Basking Ridge, NJ 07920.

8106706 Revised: January 2026

This Patient Information has been approved by the U.S. Food and Drug Administration.

PACKAGE LABEL.PRINCIPAL DISPLAY PANEL

Sildenafil Tablets 20 mg (Indrad)

Sildenafil Tablets 20 mg (Dahej)